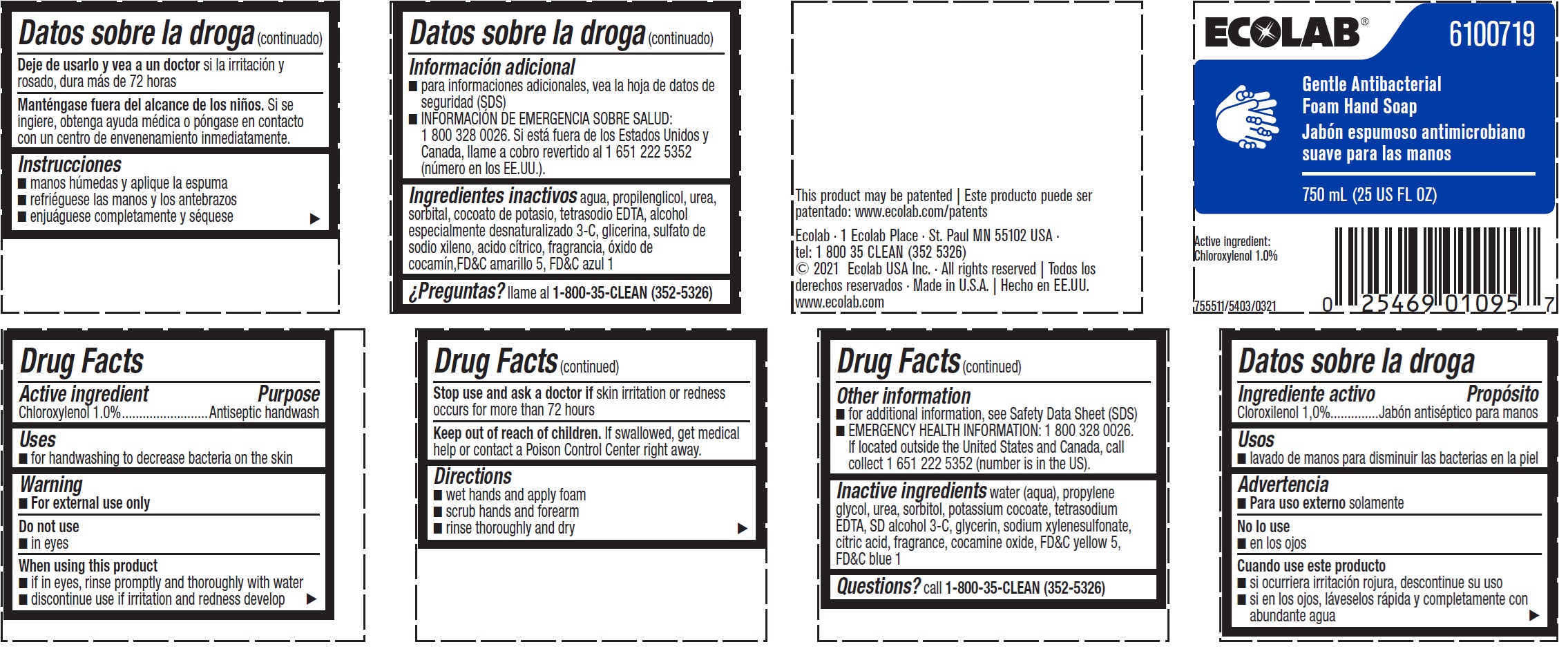 DRUG LABEL: Ecolab
NDC: 47593-506 | Form: LIQUID
Manufacturer: Ecolab Inc.
Category: otc | Type: HUMAN OTC DRUG LABEL
Date: 20240709

ACTIVE INGREDIENTS: CHLOROXYLENOL 10 mg/1 mL
INACTIVE INGREDIENTS: WATER; PROPYLENE GLYCOL; UREA; SORBITOL; POTASSIUM COCOATE; EDETATE SODIUM; ALCOHOL; GLYCERIN; SODIUM XYLENESULFONATE; CITRIC ACID MONOHYDRATE; COCAMINE OXIDE; FD&C YELLOW NO. 5; FD&C BLUE NO. 1; ISOPROPYL ALCOHOL

Drug Facts

Active ingredient

Chloroxylenol 1.0%

Purpose

Antiseptic handwash

Uses

- For handwashing to decrease bacteria on the skin

Warnings

For external use only

Do not use

- In eyes

When using this product

- If in eyes, rinse promptly and thoroughly with water
- Discontinue use if irritation and redness develop

Stop use and ask a doctor if

- Skin irritation or redness occurs for more for 72 hours

Keep out of reach of children. If swallowed, get medical help or contact a Poison Control Center right away.

Directions

- Wet hands and apply foam
- Scrub hands and forearm
- Rinse thoroughly and dry

Other information

- For additional information, see Safety Data Sheet (SDS)
- EMERGENCY HEALTH INFORMATION: 1 800 328 0026. If located outside the United States and Canada, call collect 1 651 222 5352 (number is in the US).

INACTIVE INGREDIENT

Inactive ingredients water (aqua), propylene glycol, urea, sorbitol, potassium cocoate, tetrasodium EDTA, SD alcohol 3-C, glycerin, sodium xylenesulfonate, citric acid, fragrance, cocamine oxide, FDC yellow 5, FDC blue 1

Questions? call 1.800.35.CLEAN (352.5326)

Principal Display Panel and Representative Label

ECOLAB®

6100719

Gentle Antibacterial

Foam Hand Soap

750 ML (25 US FL OZ)

Active ingredient: Chloroxylenol 1.0%

755511/5403/0321

Ecolab · 1 Ecolab Place · St. Paul MN 55102 USA

tel: 1 800 35 CLEAN (352 5326)

© 2021 Ecolab USA Inc. · All rights reserved

Made in U.S.A.